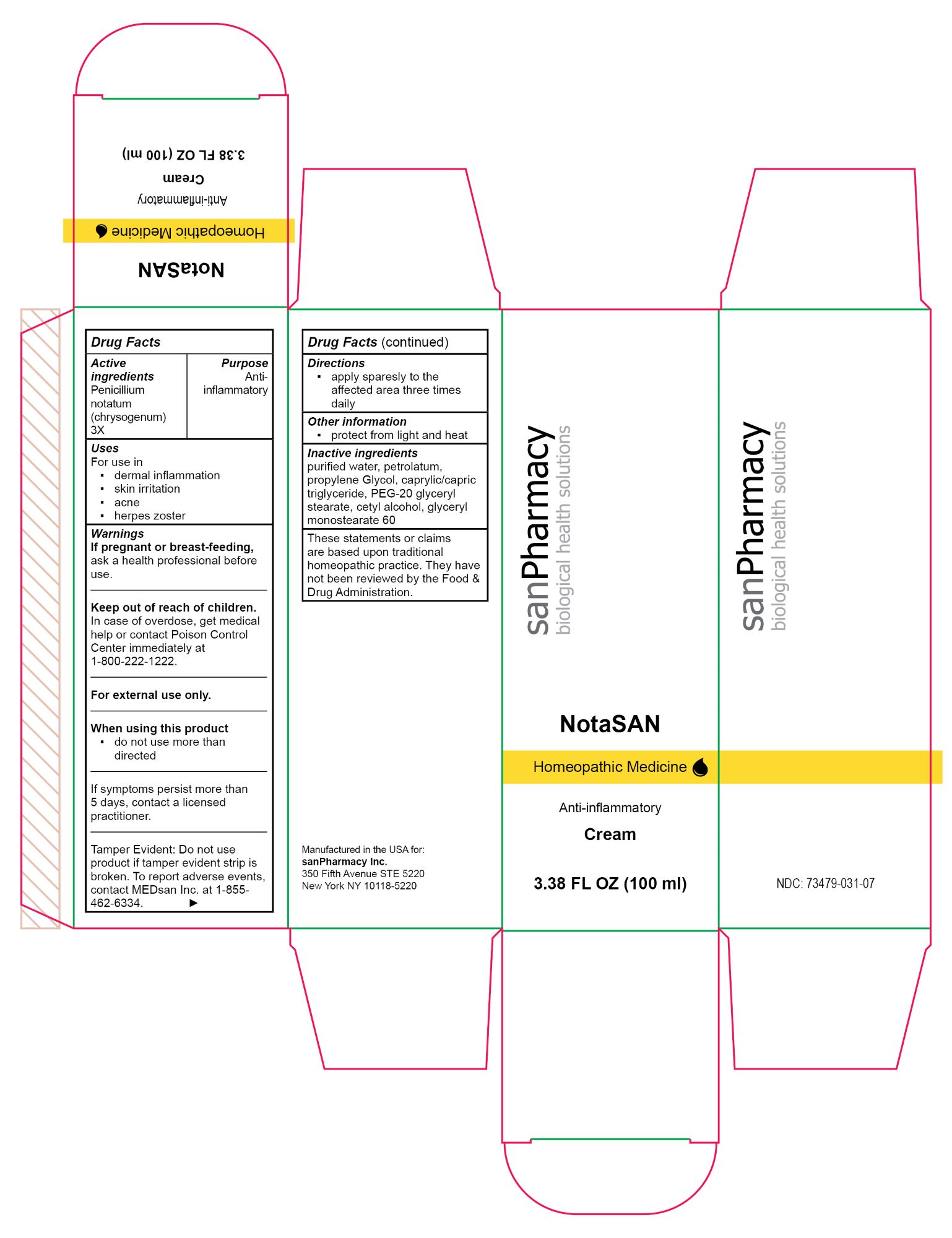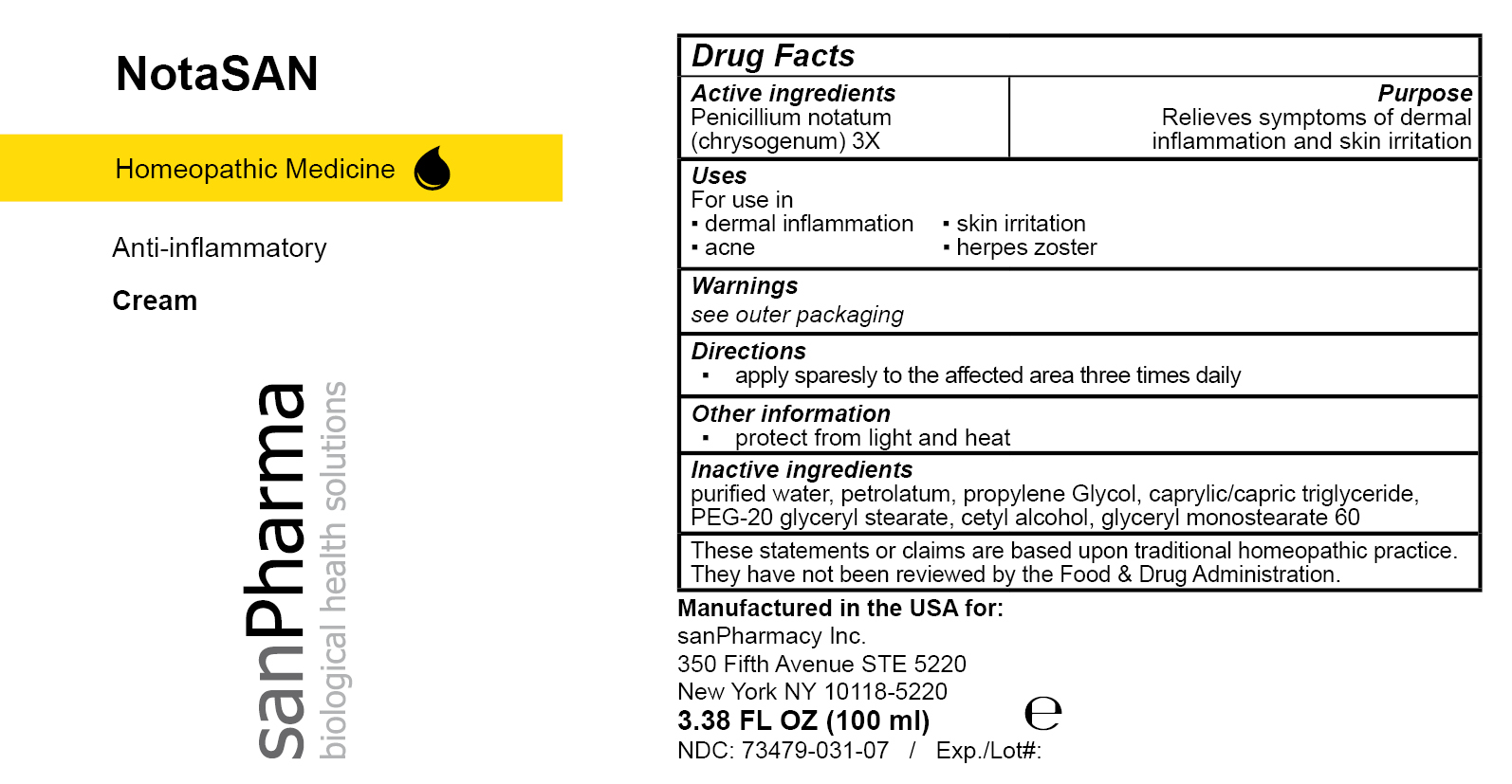 DRUG LABEL: NotaSAN
NDC: 73479-031 | Form: CREAM
Manufacturer: sanPharmacy Inc.
Category: homeopathic | Type: HUMAN OTC DRUG LABEL
Date: 20240502

ACTIVE INGREDIENTS: PENICILLIUM CHRYSOGENUM VAR. CHRYSOGENUM 3 [hp_X]/100 mL
INACTIVE INGREDIENTS: PEG-20 GLYCERYL STEARATE; PROPYLENE GLYCOL; GLYCERYL MONOSTEARATE; PETROLATUM; MEDIUM-CHAIN TRIGLYCERIDES; CETYL ALCOHOL; WATER

NotaSAN Cream

Indications

Anti-inflammatory

Purpose

Relieves symptoms of dermal inflammation and skin irritation

Active ingredients

Penicillium notatum (chrysogenum) 3X

Inactive ingeredients

purified water, petrolatum, propylene Glycol, caprylic/capric triglyceride, PEG-20 glyceryl stearate, cetyl alcohol, glyceryl monostearate 60

Dosage

apply sparesly to the affected area three times daily

Warnings

If pregnant or breast-feeding, ask a health professional before use.
______________________________
Keep out of reach of children. In case of ingestion call Poison Control Center hotline immediately at 1-800-222-1222.
______________________________
For external use only.
______________________________
When using this product
▪ do not use more than directed
______________________________
If symptoms persist more than 5 days, contact a licensed practitioner.
______________________________
Tamper Evident: Do not use product if tamper evident strip is broken. To report adverse events, contact MEDsan Inc. at 1-855-462-6334.

Keep out of reach of children. In case of ingestion call Poison Control Center hotline immediately at 1-800-222-1222

Liability statement

These statements or claims are based upon traditional homeopathic practice. They have not been reviewed by the Food & Drug Administration

Manufactured in the USA for:
sanPharmacy Inc.
350 Fifth Avenue STE 5220
New York NY 10118-5220

STORAGE AND HANDLING

protect from light and heat

PACKAGE LABEL

NotaSAN

Homeopathic Medicine

Anti-inflammatory

Cream

3.38 FL OZ (100 ml)

sanPharmacy

biological health solutions